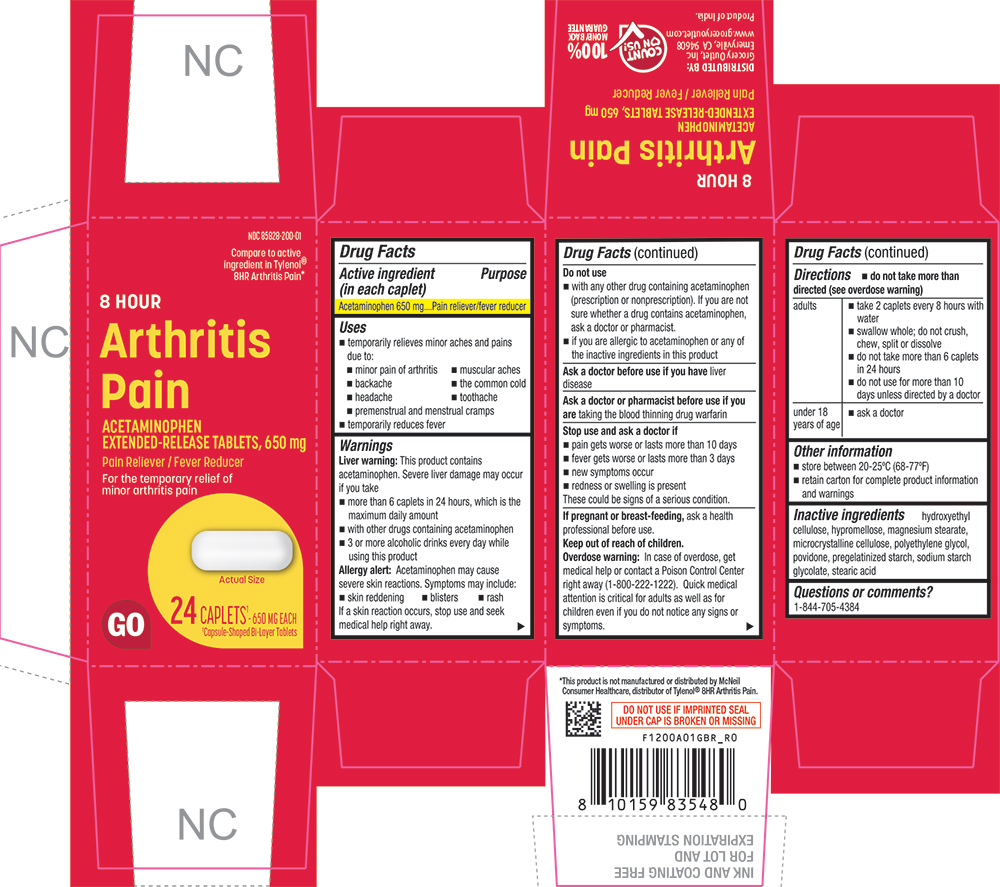 DRUG LABEL: Arthritis Pain
NDC: 85828-200 | Form: TABLET, EXTENDED RELEASE
Manufacturer: Grocery Outlet, Inc.
Category: otc | Type: HUMAN OTC DRUG LABEL
Date: 20260218

ACTIVE INGREDIENTS: ACETAMINOPHEN 650 mg/1 1
INACTIVE INGREDIENTS: HYDROXYETHYL CELLULOSE (140 MPA.S AT 5%); HYPROMELLOSE 2910 (6 MPA.S); MAGNESIUM STEARATE; CELLULOSE, MICROCRYSTALLINE; POLYETHYLENE GLYCOL 400; POVIDONE K30; STARCH, CORN; SODIUM STARCH GLYCOLATE TYPE A CORN; STEARIC ACID

1200A-GBR-2026-0218

Drug Facts

Active ingredient (in each caplet)

Acetaminophen 650 mg

Purpose

Pain reliever/fever reducer

Uses

- temporarily relieves minor aches and pains due to:
  - minor pain of arthritis
  - muscular aches
  - backache
  - premenstrual and menstrual cramps
  - the common cold
  - headache
  - toothache
- temporarily reduces fever

Warnings

Liver warning

This product contains acetaminophen. Severe liver damage may occur if you take

- more than 6 caplets in 24 hours, which is the maximum daily amount
- with other drugs containing acetaminophen
- 3 or more alcoholic drinks every day while using this product

Allergy alert

Acetaminophen may cause severe skin reactions. Symptoms may include:

- skin reddening
- blisters
- rash

If a skin reaction occurs, stop use and seek medical help right away.

Do not use

- with any other drug containing acetaminophen (prescription or nonprescription). If you are not sure whether a drug contains acetaminophen, ask a doctor or pharmacist.
- if you are allergic to acetaminophen or any of the inactive ingredients in this product

Ask a doctor before use if you haveliver disease

Ask a doctor or pharmacist before use if you aretaking the blood thinning drug warfarin

Stop use and ask a doctor if

- pain gets worse or lasts more than 10 days
- fever gets worse or lasts more than 3 days
- new symptoms occur
- redness or swelling is present

These could be signs of a serious condition.

PREGNANCY OR BREAST FEEDING

If pregnant or breast-feeding,ask a health professional before use.

Keep out of reach of children.

Overdose warning

In case of overdose, get medical help or contact a Poison Control Center right away (1-800-222-1222). Quick medical attention is critical for adults as well as for children even if you do not notice any signs or symptoms.

Directions

- do not take more than directed (see overdose warning)

adults | - take 2 caplets every 8 hours with water - swallow whole; do not crush, chew, split or dissolve - do not take more than 6 caplets in 24 hours, unless directed by a doctor - do not use for more than 10 days unless directed by a doctor
under 18 years of age | - ask a doctor

Other information

- store between 20-25°C (68-77°F)
- retain carton for complete product information and warnings

Inactive ingredients

hydroxyethyl cellulose, hypromellose, magnesium stearate, microcrystalline cellulose, polyethylene glycol, povidone, pregelatinized starch, sodium starch glycolate, stearic acid

Questions or comments?

1-844-705-4384

PRINCIPAL DISPLAY PANEL

NDC-85828-200-01

Compare to active ingredient in Tylenol® 8HR Arthritis Pain*

8 HOUR

Arthritis Pain

ACETAMINOPHEN

EXTENDED-RELEASE TABLETS, 650 mg

Pain Reliever / Fever Reducer

For the temporary relief of minor arthritis pain

Actual Size

GO

24 CAPLETS† - 650 MG EACH

†Capsule-Shaped Bi-Layer Tablets